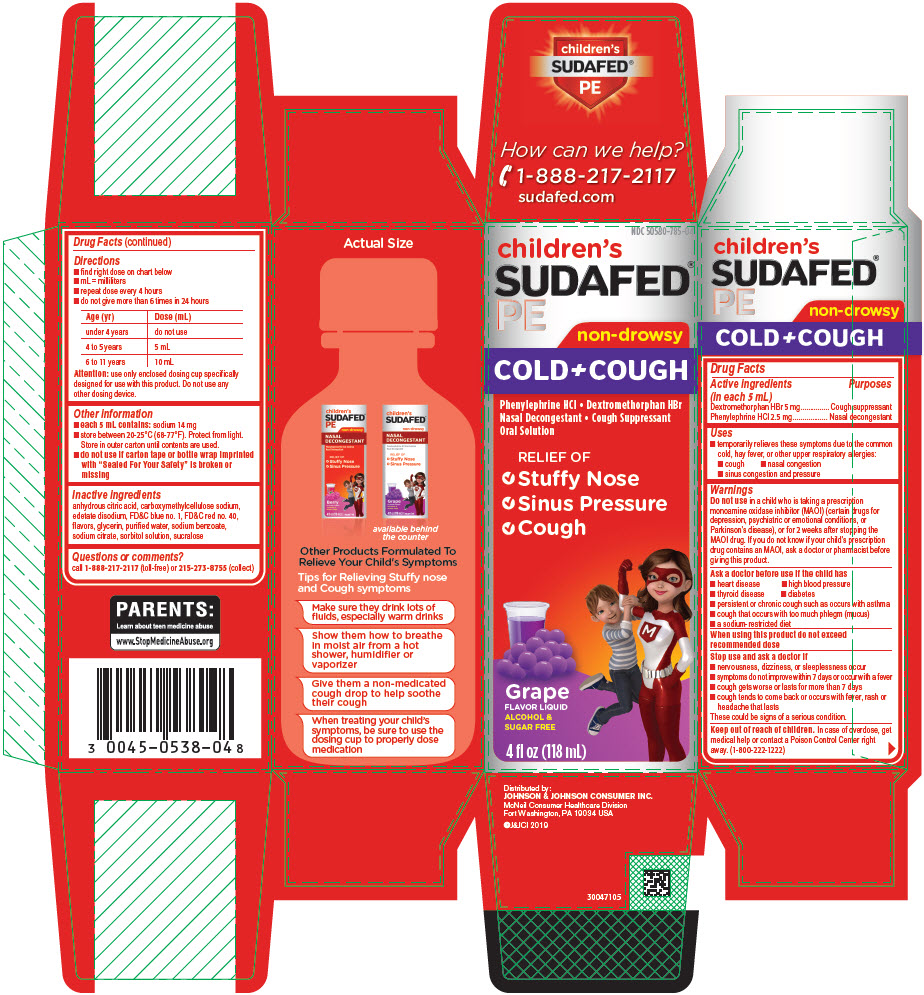 DRUG LABEL: Childrens SUDAFED PE Cold plus Cough
NDC: 50580-785 | Form: SOLUTION
Manufacturer: Kenvue Brands LLC
Category: otc | Type: HUMAN OTC DRUG LABEL
Date: 20241112

ACTIVE INGREDIENTS: DEXTROMETHORPHAN HYDROBROMIDE 5 mg/5 mL; PHENYLEPHRINE HYDROCHLORIDE 2.5 mg/5 mL
INACTIVE INGREDIENTS: ANHYDROUS CITRIC ACID; CARBOXYMETHYLCELLULOSE SODIUM, UNSPECIFIED; EDETATE DISODIUM; FD&C BLUE NO. 1; FD&C RED NO. 40; GLYCERIN; WATER; SODIUM BENZOATE; SODIUM CITRATE, UNSPECIFIED FORM; SORBITOL SOLUTION; SUCRALOSE

Children's SUDAFED PE Cold plus Cough

Drug Facts

ACTIVE INGREDIENT

PURPOSE

Active ingredients (in each 5 mL) | Purposes
Dextromethorphan HBr 5 mg | Cough suppressant
Phenylephrine HCl 2.5 mg | Nasal decongestant

Uses

- temporarily relieves these symptoms due to the common cold, hay fever, or other upper respiratory allergies:
  - cough
  - nasal congestion
  - sinus congestion and pressure

Warnings

Do not use in a child who is taking a prescription monoamine oxidase inhibitor (MAOI) (certain drugs for depression, psychiatric or emotional conditions, or Parkinson's disease), or for 2 weeks after stopping the MAOI drug. If you do not know if your child's prescription drug contains an MAOI, ask a doctor or pharmacist before giving this product.

Ask a doctor before use if the child has

- heart disease
- high blood pressure
- thyroid disease
- diabetes
- persistent or chronic cough such as occurs with asthma
- cough that occurs with too much phlegm (mucus)
- a sodium-restricted diet

When using this product do not exceed recommended dose

Stop use and ask a doctor if

- nervousness, dizziness, or sleeplessness occur
- symptoms do not improve within 7 days or occur with a fever
- cough gets worse or lasts for more than 7 days
- cough tends to come back or occurs with fever, rash or headache that lasts

These could be signs of a serious condition.

Keep out of reach of children. In case of overdose, get medical help or contact a Poison Control Center right away. (1-800-222-1222)

Directions

- find right dose on chart below
- mL = milliliters
- repeat dose every 4 hours
- do not give more than 6 times in 24 hours

Age (yr) | Dose (mL)
under 4 years | do not use
4 to 5 years | 5 mL
6 to 11 years | 10 mL

Attention: use only enclosed dosing cup specifically designed for use with this product. Do not use any other dosing device.

Other information

- each 5 mL contains: sodium 14 mg
- store between 20-25°C (68-77°F). Protect from light. Store in outer carton until contents are used.
- do not use if carton tape or bottle wrap imprinted with "Sealed For Your Safety" is broken or missing

Inactive ingredients

anhydrous citric acid, carboxymethylcellulose sodium, edetate disodium, FD&C blue no. 1, FD&C red no. 40, flavors, glycerin, purified water, sodium benzoate, sodium citrate, sorbitol solution, sucralose

Questions or comments?

call 1-888-217-2117 (toll-free) or 215-273-8755 (collect)

PRINCIPAL DISPLAY PANEL

NDC 50580-785-04

children's
SUDAFED®
PE

non-drowsy
COLD + COUGH

Phenylephrine HCl • Dextromethorphan HBr
Nasal Decongestant • Cough Suppressant
Oral Solution

RELIEF OF

- Stuffy Nose
- Sinus Pressure
- Cough

Grape
FLAVOR LIQUID
ALCOHOL &
SUGAR FREE

4 ﬂ oz (118 mL)